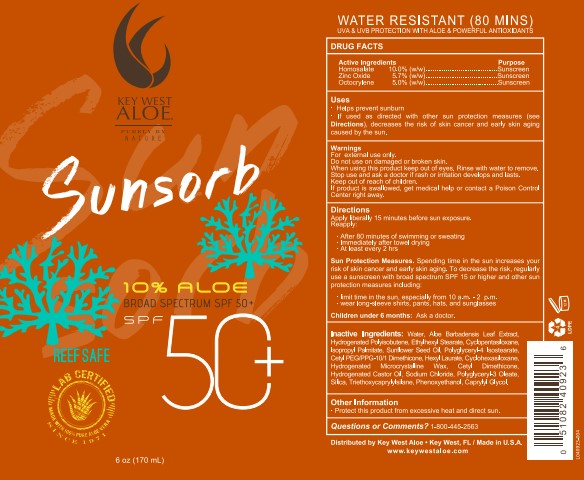 DRUG LABEL: Sunsorb Reef Safe SPF50
NDC: 65008-007 | Form: LOTION
Manufacturer: QS Key West Aloe, LLC
Category: otc | Type: HUMAN OTC DRUG LABEL
Date: 20251111

ACTIVE INGREDIENTS: HOMOSALATE 100 mg/1 g; ZINC OXIDE 57 mg/1 g; OCTOCRYLENE 50 mg/1 g
INACTIVE INGREDIENTS: WATER; ALOE VERA LEAF; HYDROGENATED POLYBUTENE (1300 MW); POLYGLYCERYL-4 ISOSTEARATE; CYCLOMETHICONE; OCTYL STEARATE; ISOPROPYL PALMITATE; SUNFLOWER OIL; CETOSTEARYL ALCOHOL; CETYL PEG/PPG-10/1 DIMETHICONE (HLB 1.5); CETYL DIMETHICONE 150; HYDROGENATED CASTOR OIL; SODIUM CHLORIDE; POLYGLYCERYL-3 OLEATE; SILICON DIOXIDE; HEXYL LAURATE; TRIETHOXYCAPRYLYLSILANE; CAPRYLYL GLYCOL; METHYLISOTHIAZOLINONE

SunsorbReef Safe SPF50

Active Ingredients

Homosalate 10.0% w/w

Zinc Oxide 5.7% w/w

Octocrylene 5.0% w/w

Purpose

Sunscreen

Uses

- Helps prevent sunburn

- If used as directed with other sun protection measures (see Directions), decreases the risk of skin cancer and early skin aging caused by the sun

Warnings

For external use only

Do not useon damaged or broken skin

When using this product

- Keep out of eyes. Rinse with water to remove.

Stop use and ask a doctor if

- Rash or irritation develops and lasts

Keep out of reach of children.

- If product is swallowed, get medical help or contact a Poison Control Center right away.

Directions

- Apply liberally 15 minutes before sun exposure

- Reapply

- After 80 minutes of swimming or sweating

- Immediately after towel drying

- At least every 2 hrs

- Sun Protection Measures. Spending time in the sun increases your risk of skin cancer and early skin aging. To decrease the risk, regularly use a sunscreen with broad spectrum SPF 15 or higher and other skin protection measures including:

- limit time in the sun, especially from 10 a.m. - 2 p.m.

- wear long-sleeve shirts, pants, hats, and sunglasses

- Children under 6 months: Ask a doctor

Inactive Ingredients:

Water, Aloe Barbadensis Leaf Extract, Hydrogenated Polybutene, Polyglyceryl-4-Isostearate, Cyclomethicone, Octyl Stearate, Isopropyl Palmitate, Sunflower Oil, Emulsifying Wax, Cetyl Dimethicone Copolyol, Cetyl Dimethicone, Hydrogenated Castor Oil, Sodium Chloride, Polyglyceryl-3 Oleate, Silica, Hexyl Laurate, Triethoxycaprylylsilane, Caprylyl Glycol, Methylisothiazolinone.

Other Information

- Protect this product from excessive heat and direct sun.

Questions or Comments?

1-800-445-2563